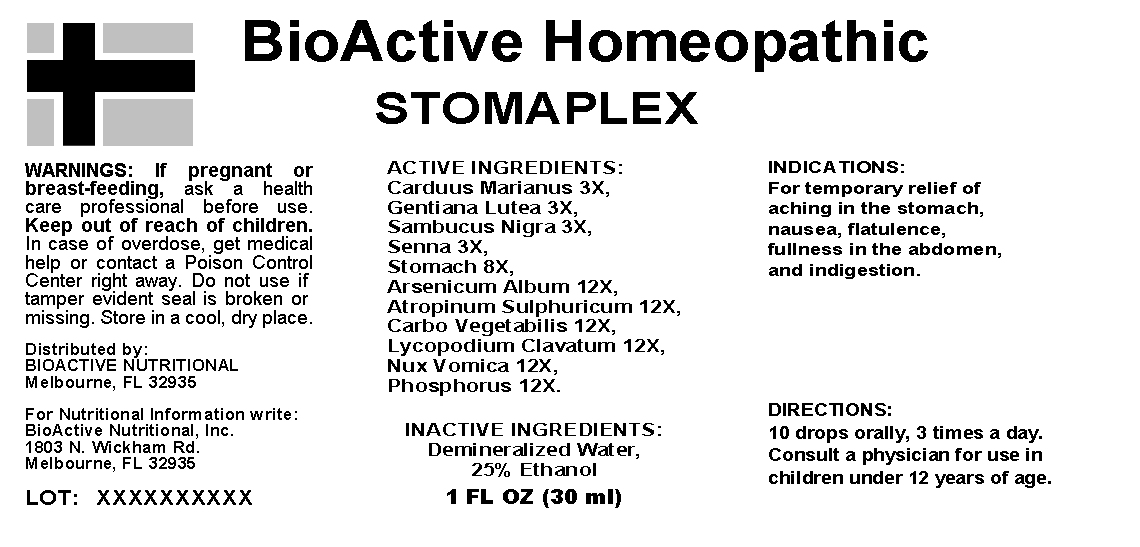 DRUG LABEL: Stomaplex
NDC: 57520-0326 | Form: LIQUID
Manufacturer: Apotheca Company
Category: homeopathic | Type: HUMAN OTC DRUG LABEL
Date: 20100625

ACTIVE INGREDIENTS: GENTIANA LUTEA ROOT 3 [hp_X]/1 mL; SAMBUCUS NIGRA FLOWERING TOP 3 [hp_X]/1 mL; SENNA LEAF 3 [hp_X]/1 mL; SUS SCROFA STOMACH 8 [hp_X]/1 mL; ARSENIC TRIOXIDE 12 [hp_X]/1 mL; ATROPINE SULFATE 12 [hp_X]/1 mL; ACTIVATED CHARCOAL 12 [hp_X]/1 mL; LYCOPODIUM CLAVATUM SPORE 12 [hp_X]/1 mL; STRYCHNOS NUX-VOMICA SEED 12 [hp_X]/1 mL; PHOSPHORUS 12 [hp_X]/1 mL; SILYBUM MARIANUM SEED 3 [hp_X]/1 mL
INACTIVE INGREDIENTS: WATER; ALCOHOL

Stomaplex

ACTIVE INGREDIENT

ACTIVE INGREDIENTS: Carduus marianus 3X, Gentiana lutea 3X, Sambucus nigra 3X, Senna 3X, Stomach 8X, Arsenicum album 12X, Atropinum sulphuricum 12X, Carbo vegetabilis 12X, Lycopodium clavatum 12X, Nux vomica 12X, Phosphorus 12X.

PURPOSE

INDICATIONS: For temporary relief of aching in the stomach, nausea, flatulence, fullness in the abdomen, and indigestion.

WARNINGS

WARNINGS: If pregnant or breast-feeding, ask a health care professional before use.

Keep out of reach of children. In case of overdose, get medical help or contact a Poison Control Center right away.

Do not use if tamper evident seal is broken or missing.

Store in a cool, dry place.

DOSAGE AND ADMINISTRATION

DIRECTIONS: 10 drops orally, 3 times a day. Consult a physician for use in children under 12 years of age.

INACTIVE INGREDIENTS: Demineralized water, 25% Ethanol

QUESTIONS

Distributed By:

BioActive Nutritional

Melbourne, FL 32935

For Nutritional Information Write:

BioActive Nutritional, Inc.

1803 N. Wickham Rd.

Melbourne, FL 32935

PACKAGE LABEL

BioActive Homeopathic

STOMAPLEX

1 FL OZ (30 ML)